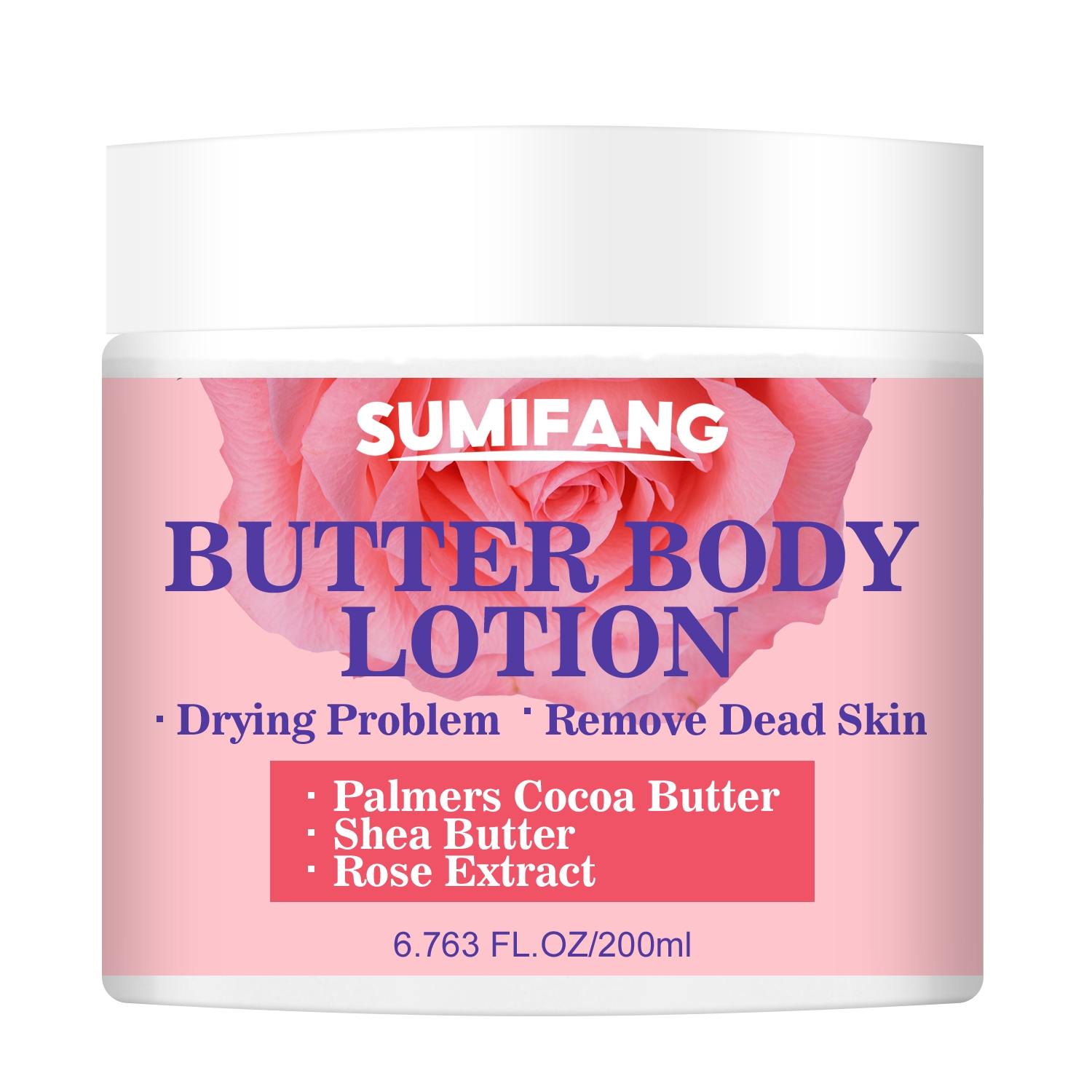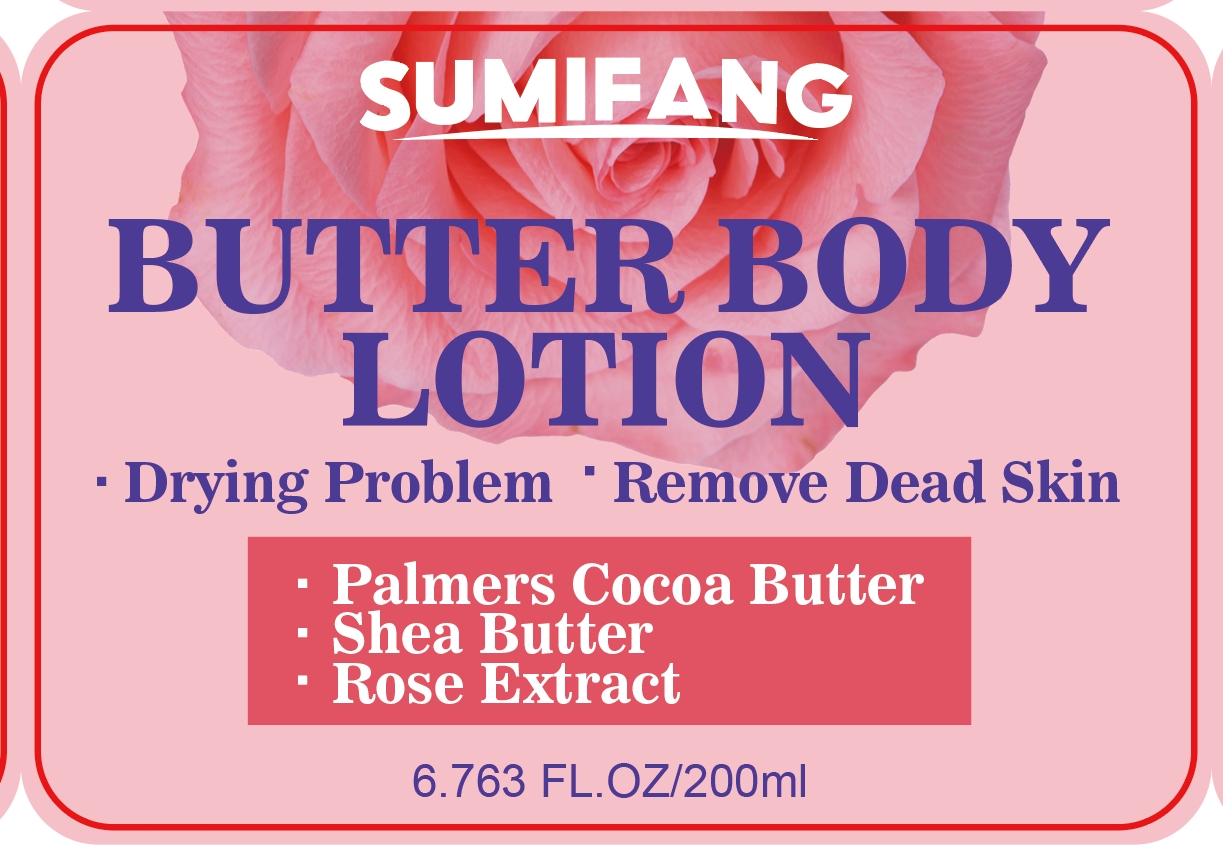 DRUG LABEL: BodyLotion
NDC: 84025-120 | Form: LOTION
Manufacturer: Guangzhou Yanxi Biotechnology Co.. Ltd
Category: otc | Type: HUMAN OTC DRUG LABEL
Date: 20240806

ACTIVE INGREDIENTS: NIACINAMIDE 5 mg/200 mL; CETEARYL OLIVATE 3 mg/200 mL
INACTIVE INGREDIENTS: WATER

DOSAGE AND ADMINISTRATION

Body Lotion for Skin Hydration

WARNINGS

Keep out of children

INACTIVE INGREDIENT

Aqua

INDICATIONS AND USAGE

For daily moisturizing of dry skin on the body

Keep out of children

PURPOSE

Moisturizes skin and addresses dryness, removes dead skin cells